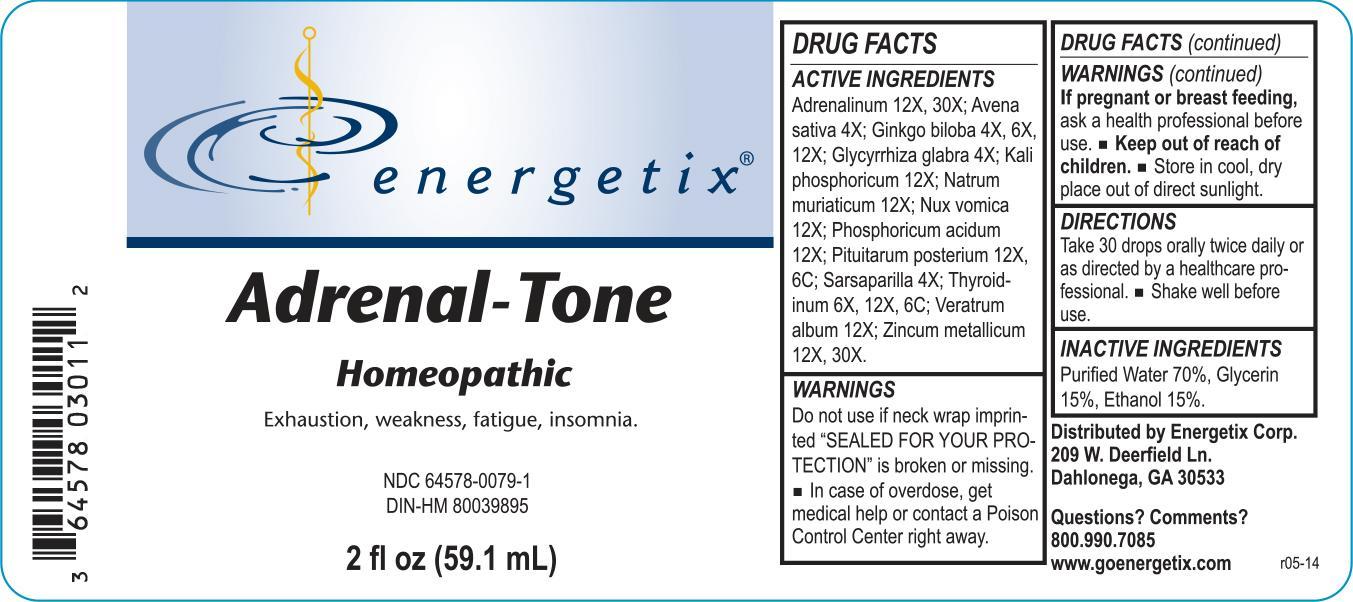 DRUG LABEL: Adrenal-Tone
NDC: 64578-0079 | Form: LIQUID
Manufacturer: Energetix Corp
Category: homeopathic | Type: HUMAN OTC DRUG LABEL
Date: 20140214

ACTIVE INGREDIENTS: EPINEPHRINE 12 [hp_X]/59.1 mL; AVENA SATIVA FLOWERING TOP 4 [hp_X]/59.1 mL; GINKGO 4 [hp_X]/59.1 mL; GLYCYRRHIZA GLABRA 4 [hp_X]/59.1 mL; POTASSIUM PHOSPHATE, DIBASIC 12 [hp_X]/59.1 mL; SODIUM CHLORIDE 12 [hp_X]/59.1 mL; STRYCHNOS NUX-VOMICA SEED 12 [hp_X]/59.1 mL; PHOSPHORIC ACID 12 [hp_X]/59.1 mL; SUS SCROFA PITUITARY GLAND 12 [hp_X]/59.1 mL; SARSAPARILLA 4 [hp_X]/59.1 mL; THYROID, UNSPECIFIED 6 [hp_X]/59.1 mL; VERATRUM ALBUM ROOT 12 [hp_X]/59.1 mL; ZINC 12 [hp_X]/59.1 mL
INACTIVE INGREDIENTS: WATER 41.358 mL/59.1 mL; ALCOHOL 8.862 mL/59.1 mL; GLYCERIN 8.862 mL/59.1 mL

Adrenal-Tone

ACTIVE INGREDIENT

Adrenalinum 12X, 30X; Avena sativa 4X; Ginkgo biloba 4X, 6X, 12X; Glycyrrhiza glabra 4X; Kali phosphoricum 12X; Natrum muriaticum 12X; Nux vomica 12X; Phosphoricum acidum 12X; Pituitarum posterium 12X, 6C; Sarsaparilla 4X; Thyroidinum 6X, 12X, 6C; Veratrum album 12X; Zincum metallicum 12X, 30X

Do not use if neck wrap imprinted "SEALED FOR YOUR PROTECTION" is broken or missing.

OVERDOSAGE

In case of overdose, get medical help or contact a Poison Control Center right away.

PREGNANCY OR BREAST FEEDING

If pregnant or breast feeding, ask a health professional before use.

Keep out of reach of children.

STORAGE AND HANDLING

Store in cool, dry place out of direct sunlight.

Questions? Comments?

800.990.7085 www.goenergetix.com

PURPOSE

Exhaustion, weakness, fatigue, insomnia.

INACTIVE INGREDIENT

Purified Water 70%, Glycerin 15%, Ethanol 15%.

DOSAGE AND ADMINISTRATION

Take 30 drops orally twice daily or as directed by a healthcare professional. Shake well before use.

INDICATIONS AND USAGE

Exhaustion, weakness, fatigue, insomnia.